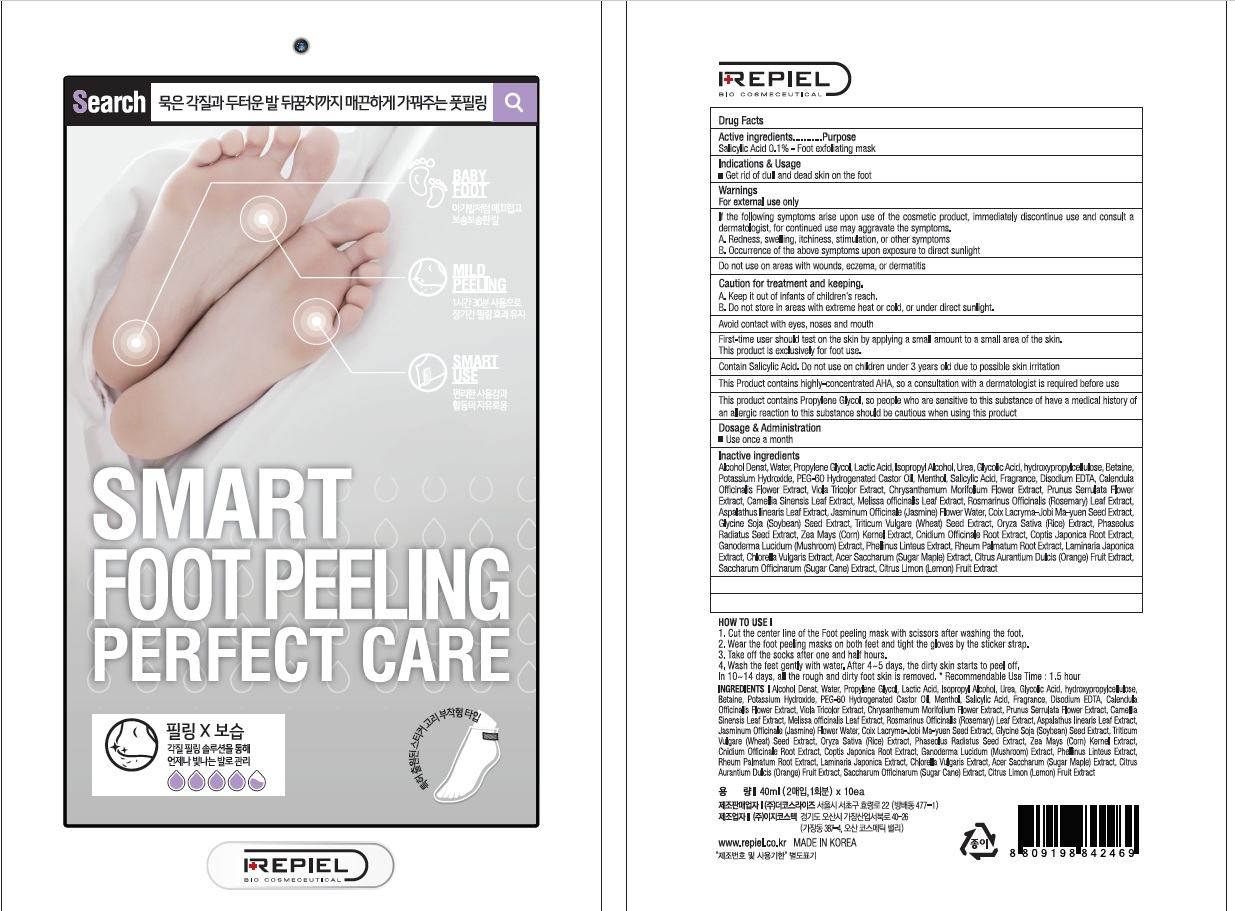 DRUG LABEL: REPIEL SMART FOOT PEELING PERFECT CARE
NDC: 70758-050 | Form: PATCH
Manufacturer: THE COSRISE CO.,LTD
Category: otc | Type: HUMAN OTC DRUG LABEL
Date: 20160629

ACTIVE INGREDIENTS: Salicylic Acid 0.04 g/40 mL
INACTIVE INGREDIENTS: Water; Propylene Glycol

ACTIVE INGREDIENT

Active Ingredient: Salicylic Acid 0.1%

INACTIVE INGREDIENT

Inactive Ingredients: Alcohol Denat, Water, Propylene Glycol, Lactic Acid, Isopropyl Alcohol, Urea, Glycolic Acid, hydroxypropylcellulose, Betaine, Potassium Hydroxide, PEG-60 Hydrogenated Castor Oil, Menthol, Salicylic Acid, Fragrance, Disodium EDTA, Calendula Officinalis Flower Extract, Viola Tricolor Extract, Chrysanthemum Morifolium Flower Extract, Prunus Serrulata Flower Extract, Camellia Sinensis Leaf Extract, Melissa officinalis Leaf Extract, Rosmarinus Officinalis (Rosemary) Leaf Extract, Aspalathus linearis Leaf Extract, Jasminum Officinale (Jasmine) Flower Water, Coix Lacryma-Jobi Ma-yuen Seed Extract, Glycine Soja (Soybean) Seed Extract, Triticum Vulgare (Wheat) Seed Extract, Oryza Sativa (Rice) Extract, Phaseolus Radiatus Seed Extract, Zea Mays (Corn) Kernel Extract, Cnidium Officinale Root Extract, Coptis Japonica Root Extract, Ganoderma Lucidum (Mushroom) Extract, Phellinus Linteus Extract, Rheum Palmatum Root Extract, Laminaria Japonica Extract, Chlorella Vulgaris Extract, Acer Saccharum (Sugar Maple) Extract, Citrus Aurantium Dulcis (Orange) Fruit Extract, Saccharum Officinarum (Sugar Cane) Extract, Citrus Limon (Lemon) Fruit Extract

PURPOSE

Purpose: Foot exfoliating mask

WARNINGS

Warnings: For external use only. 1. If the following symptoms arise upon use of the cosmetic product, immediately discontinue use and consult a dermatologist, for continued use may aggravate the symptoms. A. Redness, swelling, itchiness, stimulation, or other symptoms B. Occurrence of the above symptoms upon exposure to direct sunlight. 2. Do not use on areas with wounds, eczema, or dermatitis. 3. Caution for treatment and keeping. A. Use immediately upon opening. B. Keep it out of infants of children's reach. C. Do not store in areas with extreme heat or cold, or under direct sunlight. 4. Avoid the eye, nose and mouth area 5. First-time user should test on the skin by applying a small amount to a small area of the skin. This product is exclusively for foot use. 6. Contain Salicylic Acid. Do not use on children under 3 years old due to possible skin irritation. 7. This Product contains highly-concentrated AHA, so a consultation with a dermatologist is required before use. 8. This product contains Propylene Glycol, so people who are sensitive to this substance of have a medical history of an allergic reaction to this substance should be cautious when using this product

KEEP OUT OF REACH OF CHILDREN

Keep it out of infants of children's reach.

INDICATIONS & USAGE

Indications & Usage: Get rid of dull and dead skin on the foot

How to use: 1. Cut the center line of the Foot peeling mask with scissors after washing the foot. 2. Wear the foot peeling masks on both feet and tight the gloves by sticker strap. 3. Take off the socks after one and half hours. 4. wash the feet gently with water. After 4~5 days, the dirty skin starts to peel off. In 10~14 days, all the rough and dirty foot skin is removed. (Recommendable Use Time: 1.5 hour) *The peeling effect may depend on each person’s condition and please keep the recommendable use hour. It may get the skin hurt in case of excess of the recommendable hour.

DOSAGE & ADMINISTRATION

Dosage & Administration: Use once a month.